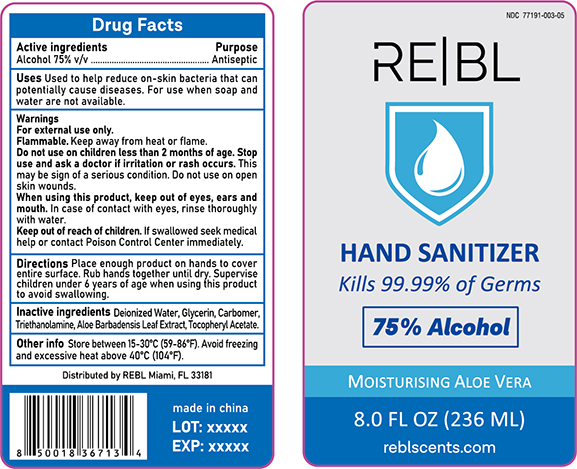 DRUG LABEL: REBL Hand Sanitizer
NDC: 77191-003 | Form: SOLUTION
Manufacturer: Yiwu Jiayan Cosmetics Co., Ltd.
Category: otc | Type: HUMAN OTC DRUG LABEL
Date: 20200521

ACTIVE INGREDIENTS: ALCOHOL 75 mL/100 mL
INACTIVE INGREDIENTS: GLYCERIN; WATER; CARBOMER 934; TROLAMINE; ALOE VERA LEAF; .ALPHA.-TOCOPHEROL ACETATE

Active Ingredient(s)

Alcohol 75% v/v

Purpose

Antiseptic

Use

To Help reduce the on skin bacteria that could cause diseases

For use when soap and water are not available

Warnings

For external use only -hands

Flammable. Keep away from heat or flame

Do not use on chaildren less than two months of age

When using this product keep out of eyes, ears, and mouth. In case of contact with eyes, rinse thoroughly with water.

Avoid contact with broken skin

Do not inhale or ingest

Stop use and ask a doctor if irritation or rash occurs. This may be sign of serioous condition. Do not use on open skin wounds

Keep out of reach of children. If swallowed seek medical help or contact a Poison Control Center immediately.

Directions

- Place enough product on hands to cover entire surface. Rub hands together until dry.
- Supervise children under 6 years old when using this product to avoid swallowing

Other information

Store between 15-30C (59-86F)

Avoid freezing and excessive heat about 40C (104F)

Inactive ingredients

Water, glycerin, carbomer, triethanolamine, aloe barbadensis leaf extract, tocopheryl acetate